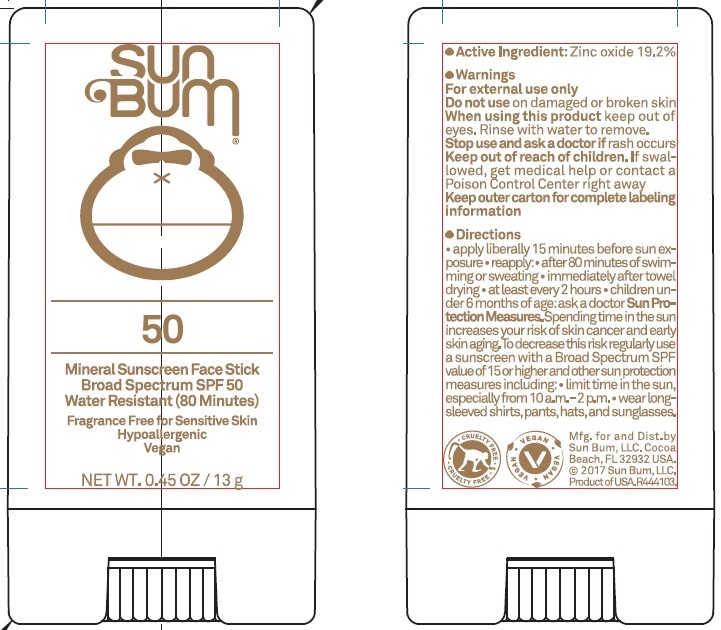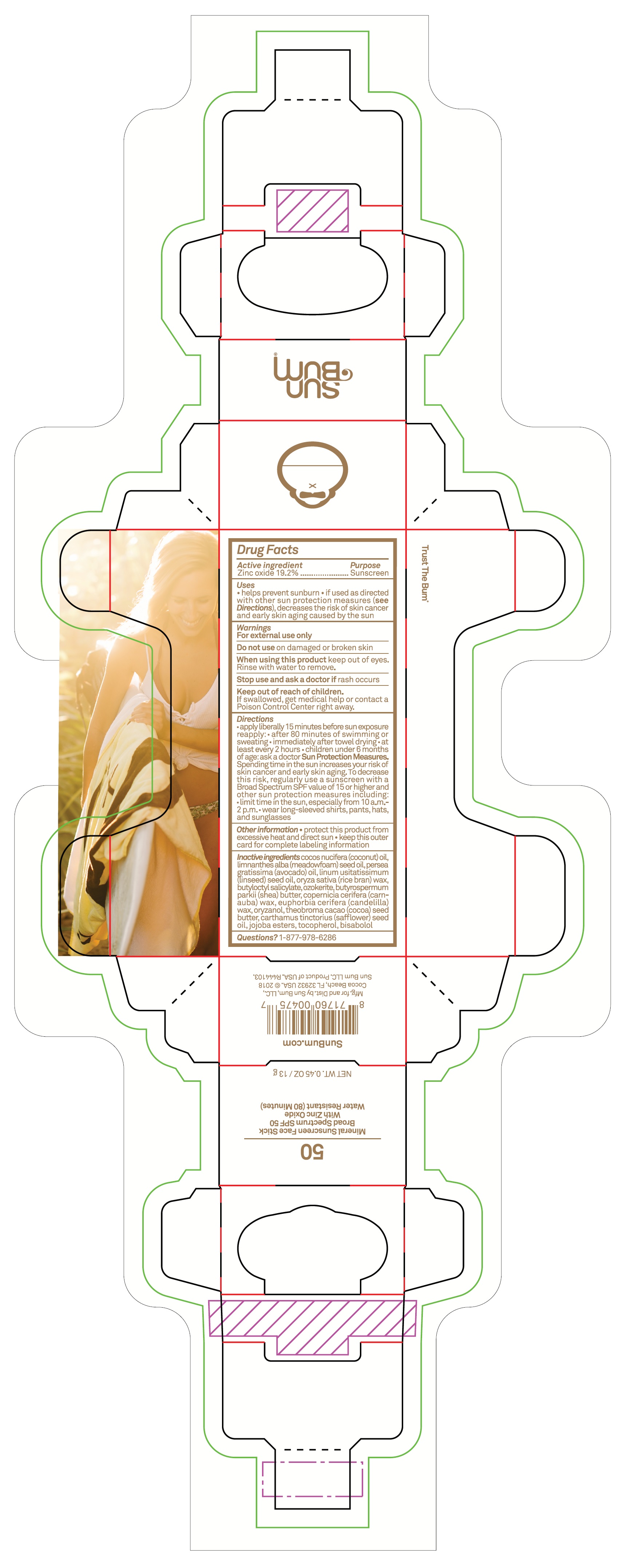 DRUG LABEL: Sun Bum Mineral Sunscreen Face Stick SPF 50
NDC: 69039-620 | Form: STICK
Manufacturer: Sun Bum LLC
Category: otc | Type: HUMAN OTC DRUG LABEL
Date: 20220204

ACTIVE INGREDIENTS: ZINC OXIDE 192 mg/1 g
INACTIVE INGREDIENTS: CERESIN; COCONUT OIL; MEADOWFOAM SEED OIL; AVOCADO OIL; LINSEED OIL; BUTYLOCTYL SALICYLATE; SHEA BUTTER; CARNAUBA WAX; CANDELILLA WAX; ORYZANOL; COCOA BUTTER; SAFFLOWER OIL; TOCOPHEROL; LEVOMENOL

Sun Bum Mineral Sunscreen Face Stick SPF 50

Active ingredient

Zinc oxide 19.2%

Purpose

Sunscreen

Uses

- helps prevent sunburn
- if used as directed with other sun protection measures (see Directions), decreases the risk of skin cancer and early skin aging caused by the sun

Warnings

- For external use only

Do not use

- on damaged or broken skin

When using this product

- keep out of eyes. Rinse with water to remove.

Stop use and ask a doctor if

- rash occurs

Keep out of reach of children.

- If swallowed, get medical help or contact a Poison Control Center right away.

Directions

- apply liberally 15 minutes before sun exposure.
- reapply: After 80 minutes of swimming or sweating, immediately after towel drying
- at least every 2 hours.
- children under 6 months of age: ask a doctor.
- Sun Protections Measures- Spending time in the sun increases your risk of skin cancer and early skin aging. To decrease this risk, regurlarly use a sunscreen with a Broad Spectrum SPF value of 15 or higher and other sun protection measures including:
- limit time in the sun, especially from 10 a.m. - 2 p.m.
- wear long-sleeved shirts, pants, hats, and sunglasses

Other information

- protect this product from excessive heat and direct sun.
- keep this outer card for complete labeling information

Inactive ingredients

cocos nucifera (coconut) oil, limnathes alba (meadowfoam) seed oil, persea gratiima (avocado) oil, linum usitatissimum (linseed) seed oil, oryza sativa (rice bran) wax, butyloctyl salicylate, ozokerite, butyrospermum parkii (shea) butter, copernicia cerifera (carn-auba) wax, euphorbia cerifera (candelilla) wax, oryzanol, theobroma cacoa (cocoa) seed butter, carthamus tinctorius (sufflower) seed oil, jojoba esters, tocopherol, bisabolol

Questions?

1-877-978-6286